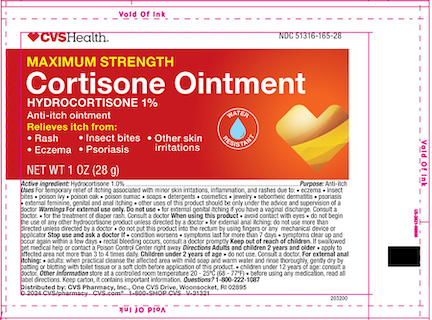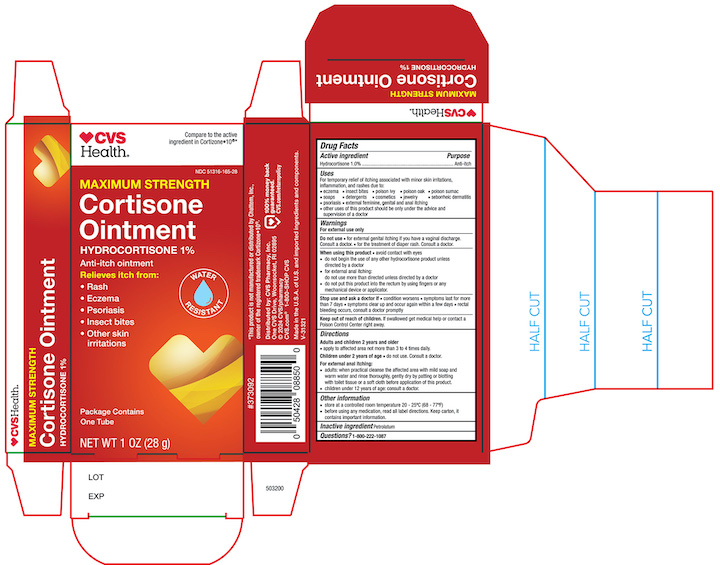 DRUG LABEL: CVS Health Maximum Strength Hydrocortisone
NDC: 51316-165 | Form: OINTMENT
Manufacturer: CVS Health
Category: otc | Type: HUMAN OTC DRUG LABEL
Date: 20240802

ACTIVE INGREDIENTS: HYDROCORTISONE 10 mg/1 g
INACTIVE INGREDIENTS: PETROLATUM

Active ingredient

Hydrocortisone 1%

Purpose

Anti-Itch

Uses

■ temporarily relieves itching associated with minor skin irritations, inflammation, and rashes due to:

■ eczema ■ psoriasis ■ poison ivy, oak, sumac ■ insect bites ■ detergents ■ jewelry ■ cosmetics

■ soaps ■ seborrheic dermatitis

■ temporarily relieves external anal and genital itching

■ other uses of this product should only be under the advice and supervision of a doctor

Warnings

For external use only

Do not use

■ in the genital area if you have a vaginal discharge. Consult a doctor. ■ for the treatment of diaper rash. Consult a doctor.

When using this product

■ avoid contact with eyes ■ do not use more than directed unless told to do so by a doctor ■ do not put directly into the rectum by using fingers or any mechanical device or applicator

Stop use and ask a Doctor if

■ condition worsens, symptoms persist for more than 7 days or clear up and occur again within a few days, and do not begin use of any other hydrocortisone product unless you have asked a doctor

Keep out of reach of children.
If swallowed, get medical help or contact a Poison Control Center right away.

Directions

- adults and children 2 years of age and older: apply to affected area not more than 3 to 4 time daily
- children under 2 years of age: ask a doctor

for external anal itching,

- adults:when practical, clean the affected area with mild soap and warm water and rinse thoroughlygently dry by patting or blotting with toilet tissue or a soft cloth before applying

apply to affected area not more than 3 to 4 times daily

- children under 12 years of age: ask a doctor

Other information

- Store at a controlled room temperature 20-25°C (68-77°F)
- before using any medication read all label direction, keep carton it contains important information

Inactive ingredient

Petrolatum

Principal Display Panel

CVS NDC 51316-165-28

Maximum strength

Cortisone Ointment

Hydrocortisone 1%

NET WT 1.0 OZ (28g)